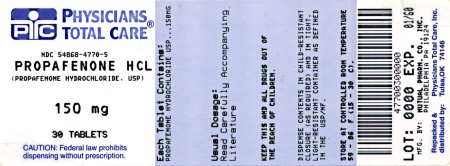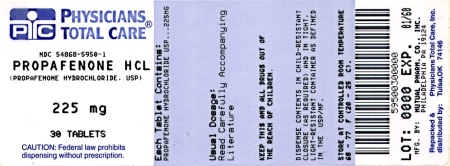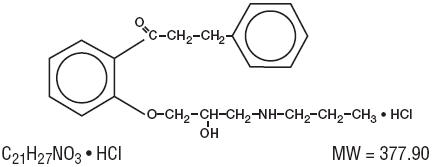 DRUG LABEL: Propafenone Hydrochloride
NDC: 54868-4770 | Form: TABLET, FILM COATED
Manufacturer: Physicians Total Care, Inc.
Category: prescription | Type: HUMAN PRESCRIPTION DRUG LABEL
Date: 20131206

ACTIVE INGREDIENTS: PROPAFENONE HYDROCHLORIDE 150 mg/1 1
INACTIVE INGREDIENTS: CARNAUBA WAX; HYPROMELLOSES; MAGNESIUM STEARATE; POLYDEXTROSE; POLYETHYLENE GLYCOLS; POLYSORBATE 80; POVIDONE; STARCH, CORN; PROPYLENE GLYCOL; SODIUM STARCH GLYCOLATE TYPE A POTATO; TITANIUM DIOXIDE; TRIACETIN

PROPAFENONE HYDROCHLORIDE TABLETS

Rx only

DESCRIPTION

Propafenone hydrochloride is an antiarrhythmic drug supplied in scored, film-coated tablets of 150, 225 and 300 mg for oral administration. Propafenone has some structural similarities to beta-blocking agents.

The structural formula of propafenone hydrochloride is given below:

2'-[2-Hydroxy-3-(propylamino)-propoxy]-3-phenylpropiophenone hydrochloride

Propafenone hydrochloride occurs as colorless crystals or white crystalline powder with a very bitter taste. It is slightly soluble in water (20°C), chloroform and ethanol. The following inactive ingredients are contained in the tablet: carnauba wax, hypromellose, magnesium stearate, polydextrose, polyethylene glycol, polysorbate 80, povidone, pregelatinized starch (corn), propylene glycol, sodium starch glycolate, titanium dioxide, and triacetin.

CLINICAL PHARMACOLOGY

Mechanism of Action

Propafenone is a Class 1C antiarrhythmic drug with local anesthetic effects, and a direct stabilizing action on myocardial membranes. The electrophysiological effect of propafenone manifests itself in a reduction of upstroke velocity (Phase 0) of the monophasic action potential. In Purkinje fibers, and to a lesser extent myocardial fibers, propafenone reduces the fast inward current carried by sodium ions. Diastolic excitability threshold is increased and effective refractory period prolonged. Propafenone reduces spontaneous automaticity and depresses triggered activity.

Studies in anesthetized dogs and isolated organ preparations show that propafenone has beta-sympatholytic activity at about 1/50 the potency of propranolol. Clinical studies employing isoproterenol challenge and exercise testing after single doses of propafenone indicate a beta-adrenergic blocking potency (per mg) about 1/40 that of propranolol in man. In clinical trials, resting heart rate decreases of about 8% were noted at the higher end of the therapeutic plasma concentration range. At very high concentrations in vitro, propafenone can inhibit the slow inward current carried by calcium, but this calcium antagonist effect probably does not contribute to antiarrhythmic efficacy. Propafenone has local anesthetic activity approximately equal to procaine.

Electrophysiology

Electrophysiology studies in patients with ventricular tachycardia (VT) have shown that propafenone HCl prolongs atrioventricular (AV) conduction while having little or no effect on sinus node function. Both AV nodal conduction time (AH interval) and His-Purkinje conduction time (HV interval) are prolonged. Propafenone has little or no effect on the atrial functional refractory period, but AV nodal functional and effective refractory periods are prolonged. In patients with Wolff-Parkinson-White (WPW) syndrome, propafenone reduces conduction and increases the effective refractory period of the accessory pathway in both directions. Propafenone slows conduction and consequently produces dose-related changes in the PR interval and QRS duration. QTc interval does not change.

Mean Changes in ECG Intervals [Change and percent change based on mean baseline values for each treatment group.]
Total Daily Dose (mg)
 | 337.5 mg |  | 450 mg |  | 675 mg |  | 900 mg
Interval | msec | % | msec | % | msec | % | msec | %
RR | −14.5 | −1.8 | 30.6 | 3.8 | 31.5 | 3.9 | 41.7 | 5.1
PR | 3.6 | 2.1 | 19.1 | 11.6 | 28.9 | 17.8 | 35.6 | 21.9
QRS | 5.6 | 6.4 | 5.5 | 6.1 | 7.7 | 8.4 | 15.6 | 17.3
QTc | 2.7 | 0.7 | −7.5 | −1.8 | 5.0 | 1.2 | 14.7 | 3.7

In any individual patient, the above ECG changes cannot be readily used to predict either efficacy or plasma concentration.

Propafenone causes a dose-related and concentration-related decrease in the rate of single and multiple premature ventricular contractions (PVCs) and can suppress recurrence of ventricular tachycardia. Based on the percent of patients attaining substantial (80–90%) suppression of ventricular ectopic activity, it appears that trough plasma levels of 0.2 to 1.5 µg/mL can provide good suppression, with higher concentrations giving a greater rate of good response.

When 600 mg/day propafenone was administered to patients with paroxysmal atrial tachyarrhythmias, mean heart rate during arrhythmia decreased 14 beats/min and 37 beats/min for paroxysmal atrial fibrillation/flutter (PAF) patients and paroxysmal supraventricular tachycardia (PSVT) patients, respectively.

Hemodynamics

Sympathetic stimulation may be a vital component supporting circulatory function in patients with congestive heart failure, and its inhibition by the beta blockade produced by propafenone HCl may in itself aggravate congestive heart failure.

Additionally, like other Class 1C antiarrhythmic drugs, studies in humans have shown that propafenone HCl exerts a negative inotropic effect on the myocardium. Cardiac catheterization studies in patients with moderately impaired ventricular function (mean C.I. = 2.61 L/min/m^2) utilizing intravenous propafenone infusions (2 mg/kg over 10 min+2 mg/min for 30 min) that gave mean plasma concentrations of 3.0 µg/mL (well above the therapeutic range of 0.2–1.5 µg/mL) showed significant increases in pulmonary capillary wedge pressure, systemic and pulmonary vascular resistances and depression of cardiac output and cardiac index.

Pharmacokinetics and Metabolism

Propafenone HCl is nearly completely absorbed after oral administration with peak plasma levels occurring approximately 3.5 hours after administration in most individuals. Propafenone exhibits extensive saturable presystemic biotransformation (first pass effect) resulting in a dose dependent and dosage form dependent absolute bioavailability; e.g., a 150 mg tablet had absolute bioavailability of 3.4%, while a 300 mg tablet had absolute bioavailability of 10.6%. A 300 mg solution which was rapidly absorbed, had absolute bioavailability of 21.4%. At still larger doses, above those recommended, bioavailability increases still further. Decreased liver function also increases bioavailability; bioavailability is inversely related to indocyanine green clearance reaching 60–70% at clearances of 7 mL/min and below. The clearance of propafenone is reduced and the elimination half-life increased in patients with significant hepatic dysfunction (see PRECAUTIONS).

Propafenone HCl follows a nonlinear pharmacokinetic disposition presumably due to saturation of first pass hepatic metabolism as the liver is exposed to higher concentrations of propafenone and shows a very high degree of interindividual variability. For example, for a three-fold increase in daily dose from 300 to 900 mg/day there is a tenfold increase in steady-state plasma concentration. The top 25% of patients given 375 mg/day, however, had a mean concentration of propafenone larger than the bottom 25%, and about equal to the second 25%, of patients given a dose of 900 mg. Although food increased peak blood level and bioavailability in a single dose study, during multiple dose administration of propafenone to healthy volunteers food did not change bioavailability significantly.

There are two genetically determined patterns of propafenone metabolism. In over 90% of patients, the drug is rapidly and extensively metabolized with an elimination half-life from 2–10 hours. These patients metabolize propafenone into two active metabolites: 5-hydroxypropafenone which is formed by CYP2D6 and N-depropylpropafenone which is formed by both CYP3A4 and CYP1A2.

In vitro preparations have shown these two metabolites to have antiarrhythmic activity comparable to propafenone but in man they both are usually present in concentrations less than 20% of propafenone. Nine additional metabolites have been identified, most in only trace amounts. It is the saturable hydroxylation pathway that is responsible for nonlinear pharmacokinetic disposition.

In less than 10% of patients (and in any patient also receiving quinidine, see PRECAUTIONS), metabolism of propafenone is slower because the 5-hydroxy metabolite is not formed or is minimally formed. The estimated propafenone elimination half-life ranges from 10–32 hours. Decreased ability to form the 5-hydroxy metabolite of propafenone is associated with a diminished ability to metabolize debrisoquine and a variety of other drugs (encainide, metoprolol, dextromethorphan). In these patients, the N-depropylpropafenone occurs in quantities comparable to the levels occurring in extensive metabolizers. In slow metabolizers propafenone pharmacokinetics are linear.

There are significant differences in plasma concentrations of propafenone in slow and extensive metabolizers, the former achieving concentrations 1.5 to 2.0 times those of the extensive metabolizers at daily doses of 675–900 mg/day. At low doses the differences are greater, with slow metabolizers attaining concentrations more than five times that of extensive metabolizers. Because the difference decreases at high doses and is mitigated by the lack of the active 5-hydroxy metabolite in the slow metabolizers, and because steady-state conditions are achieved after 4–5 days of dosing in all patients, the recommended dosing regimen is the same for all patients. The greater variability in blood levels require that the drug be titrated carefully in patients with close attention paid to clinical and ECG evidence of toxicity (See DOSAGE AND ADMINISTRATION).

In vitro and in vivo studies have shown that the R-isomer of propafenone is cleared faster than the S-isomer via the 5-hydroxylation pathway (CYP2D6). This results in a higher ratio of S-propafenone during steady state.

Clinical Trials

In two randomized, crossover, placebo-controlled, double-blind trials of 60–90 days duration in patients with paroxysmal supraventricular arrhythmias [paroxysmal atrial fibrillation/flutter (PAF), or paroxysmal supraventricular tachycardia (PSVT)], propafenone reduced the rate of both arrhythmias, as shown in the following table:

 | Study 1 |  | Study 2
 | Propafenone | Placebo | Propafenone | Placebo
PAF | n=30 | n=30 | n=9 | n=9
Percent attack free | 53% | 13% | 67% | 22%
Median time to first recurrence | >98 days | 8 days | 62 days | 5 days
PSVT | n=45 | n=45 | n=15 | n=15
Percent attack free | 47% | 16% | 38% | 7%
Median time to first recurrence | >98 days | 12 days | 31 days | 8 days

The patient population in the above trials was 50% male with a mean age of 57.3 years. Fifty percent of the patients had a diagnosis of PAF and 50% had PSVT. Eighty percent of the patients received 600 mg/day propafenone. No patient died in the above 2 studies.

In U.S. long-term safety trials, 474 patients (mean age: 57.4 ± 14.5 years) with supraventricular arrhythmias [195 with PAF, 274 with PSVT and 5 with both PAF and PSVT] were treated up to 5 years (mean: 14.4 months) with propafenone. Fourteen of the patients died. When this mortality rate was compared to the rate in a similar patient population (n=194 patients; mean age: 43.0 ± 16.8 years) studied in an arrhythmia clinic, there was no age-adjusted difference in mortality. This comparison was not, however, a randomized trial and the 95% confidence interval around the comparison was large, such that neither a significant adverse or favorable effect could be ruled out.

INDICATIONS AND USAGE

In patients without structural heart disease, propafenone is indicated to prolong the time to recurrence of

- paroxysmal atrial fibrillation/flutter (PAF) associated with disabling symptoms.
- paroxysmal supraventricular tachycardia (PSVT) associated with disabling symptoms.

As with other agents, some patients with atrial flutter treated with propafenone have developed 1:1 conduction, producing an increase in ventricular rate. Concomitant treatment with drugs that increase the functional AV refractory period is recommended.

The use of propafenone HCl in patients with chronic atrial fibrillation has not been evaluated. Propafenone HCl should not be used to control ventricular rate during atrial fibrillation.

Propafenone HCl is also indicated for the treatment of

- documented ventricular arrhythmias, such as sustained ventricular tachycardia, that, in the judgment of the physician, are life-threatening. Because of the proarrhythmic effects of propafenone HCl, its use with lesser ventricular arrhythmias is not recommended, even if patients are symptomatic, and any use of the drug should be reserved for patients in whom, in the opinion of the physician, the potential benefits outweigh the risks.

Initiation of propafenone HCl treatment, as with other antiarrhythmics used to treat life-threatening ventricular arrhythmias, should be carried out in the hospital.

Propafenone HCl, like other antiarrhythmic drugs, has not been shown to enhance survival in patients with ventricular or atrial arrhythmias.

CONTRAINDICATIONS

Propafenone HCl is contraindicated in the presence of uncontrolled congestive heart failure, cardiogenic shock, sinoatrial, atrioventricular and intraventricular disorders of impulse generation and/or conduction (e.g., sick sinus node syndrome, atrioventricular block) in the absence of an artificial pacemaker, bradycardia, marked hypotension, bronchospastic disorders, manifest electrolyte imbalance, and known hypersensitivity to the drug.

WARNINGS

Mortality

In the National Heart, Lung and Blood Institute's Cardiac Arrhythmia Suppression Trial (CAST), a long-term, multi-center, randomized, double-blind study in patients with asymptomatic non-life-threatening ventricular arrhythmias who had a myocardial infarction more than six days but less than two years previously, an increased rate of death or reversed cardiac arrest rate (7.7%; 56/730) was seen in patients treated with encainide or flecainide (class 1C antiarrhythmics) compared with that seen in patients assigned to placebo (3.0%; 22/725). The average duration of treatment with encainide or flecainide in this study was ten months.

The applicability of the CAST results to other populations (e.g., those without recent myocardial infarction) or other antiarrhythmic drugs is uncertain, but at present it is prudent to consider any 1C antiarrhythmic to have a significant risk in patients with structural heart disease. Given the lack of any evidence that these drugs improve survival, antiarrhythmic agents should generally be avoided in patients with non-life-threatening ventricular arrhythmias, even if the patients are experiencing unpleasant, but not life-threatening, symptoms or signs.

Proarrhythmic Effects

Propafenone HCl, like other antiarrhythmic agents, may cause new or worsened arrhythmias. Such proarrhythmic effects range from an increase in frequency of PVCs to the development of more severe ventricular tachycardia, ventricular fibrillation or torsade de pointes; i.e., tachycardia that is more sustained or more rapid which may lead to fatal consequences. It is therefore essential that each patient given propafenone HCl be evaluated electrocardiographically and clinically prior to, and during therapy to determine whether the response to propafenone HCl supports continued treatment.

Overall in clinical trials with propafenone, 4.7% of all patients had new or worsened ventricular arrhythmia possibly representing a pro-arrhythmic event (0.7% was an increase in PVCs; 4.0% a worsening, or new appearance, of VT or ventricular fibrillation [VF]). Of the patients who had worsening of VT (4%), 92% had a history of VT and/or VT/VF, 71% had coronary artery disease, and 68% had a prior myocardial infarction. The incidence of proarrhythmia in patients with less serious or benign arrhythmias, which include patients with an increase in frequency of PVCs, was 1.6%. Although most proarrhythmic events occurred during the first week of therapy, late events also were seen and the CAST study (see above) suggests that an increased risk is present throughout treatment.

In the 474 patient U.S. multicenter trial in patients with symptomatic supraventricular tachycardia (SVT), 1.9% (9/474) of these patients experienced ventricular tachycardia (VT) or ventricular fibrillation (VF) during the study. However, in 4 of the 9 patients, the ventricular tachycardia was of atrial origin. Six of the nine patients that developed ventricular arrhythmias did so within 14 days of onset of therapy. About 2.3% (11/474) of all patients had a recurrence of SVT during the study which could have been a change in the patients' arrhythmia behavior or could represent a proarrhythmic event. Case reports in patients treated with propafenone HCl for atrial fibrillation/flutter have included increased PVCs, VT, VF, and death.

Nonallergic Bronchospasm (e.g., chronic bronchitis, emphysema)

PATIENTS WITH BRONCHOSPASTIC DISEASE SHOULD, IN GENERAL, NOT RECEIVE PROPAFENONE or other agents with beta-adrenergic-blocking activity.

Congestive Heart Failure

During treatment with oral propafenone in patients with depressed baseline function (mean ejection fraction (EF)=33.5%), no significant decreases in ejection fraction were seen. In clinical trial experience, new or worsened CHF has been reported in 3.7% of patients with ventricular arrhythmia; of those 0.9% were considered probably or definitely related to propafenone HCl. Of the patients with congestive heart failure probably related to propafenone, 80% had preexisting heart failure and 85% had coronary artery disease. CHF attributable to propafenone HCl developed rarely (<0.2%) in ventricular arrhythmia patients who had no previous history of CHF. CHF occurred in 1.9% of patients studied with PAF or PSVT.

As propafenone HCl exerts both beta blockade and a (dose-related) negative inotropic effect on cardiac muscle, patients with congestive heart failure should be fully compensated before receiving propafenone HCl. If congestive heart failure worsens, propafenone HCl should be discontinued (unless congestive heart failure is due to the cardiac arrhythmia) and, if indicated, restarted at a lower dosage only after adequate cardiac compensation has been established.

Conduction Disturbances

Propafenone HCl slows atrioventricular conduction and also causes first degree AV block. Average PR interval prolongation and increases in QRS duration are closely correlated with dosage increases and concomitant increases in propafenone plasma concentrations. The incidence of first degree, second degree, and third degree AV block observed in 2,127 ventricular arrhythmia patients was 2.5%, 0.6%, and 0.2%, respectively. Development of second or third degree AV block requires a reduction in dosage or discontinuation of propafenone HCl. Bundle branch block (1.2%) and intraventricular conduction delay (1.1%) have been reported in patients receiving propafenone. Bradycardia has also been reported (1.5%). Experience in patients with sick sinus node syndrome is limited and these patients should not be treated with propafenone.

Effects on Pacemaker Threshold

Propafenone HCl may alter both pacing and sensing thresholds of artificial pacemakers. Pacemakers should be monitored and programmed accordingly during therapy.

Hematologic Disturbances

Agranulocytosis (fever, chills, weakness, and neutropenia) has been reported in patients receiving propafenone. Generally, the agranulocytosis occurred within the first two months of propafenone therapy and upon discontinuation of therapy, the white count usually normalized by 14 days. Unexplained fever and/or decrease in white cell count, particularly during the initial three months of therapy, warrant consideration of possible agranulocytosis/granulocytopenia. Patients should be instructed to promptly report the development of any signs of infection such as fever, sore throat, or chills.

PRECAUTIONS

Hepatic Dysfunction

Propafenone is highly metabolized by the liver and should, therefore, be administered cautiously to patients with impaired hepatic function. Severe liver dysfunction increases the bioavailability of propafenone to approximately 70% compared to 3–40% for patients with normal liver function. In eight patients with moderate to severe liver disease, the mean half-life was approximately 9 hours. As a result, the dose of propafenone given to patients with impaired hepatic function should be approximately 20–30% of the dose given to patients with normal hepatic function (see DOSAGE AND ADMINISTRATION). Careful monitoring for excessive pharmacological effects (see OVERDOSAGE) should be carried out.

Renal Dysfunction

A considerable percentage of propafenone metabolites (18.5%–38% of the dose/48 hours) are excreted in the urine.

Until further data are available, propafenone HCl should be administered cautiously to patients with impaired renal function. These patients should be carefully monitored for signs of overdosage (see OVERDOSAGE).

Elevated ANA Titers

Positive ANA titers have been reported in patients receiving propafenone. They have been reversible upon cessation of treatment and may disappear even in the face of continued propafenone therapy. These laboratory findings were usually not associated with clinical symptoms, but there is one published case of drug-induced lupus erythematosis (positive rechallenge); it resolved completely upon discontinuation of therapy. Patients who develop an abnormal ANA test should be carefully evaluated and, if persistent or worsening elevation of ANA titers is detected, consideration should be given to discontinuing therapy.

Impaired Spermatogenesis

Reversible disorders of spermatogenesis have been demonstrated in monkeys, dogs and rabbits after high dose intravenous administration of propafenone HCl. Evaluation of the effects of short-term propafenone administration on spermatogenesis in 11 normal subjects suggests that propafenone HCl produced a reversible, short-term drop (within normal range) in sperm count. Subsequent evaluations in 11 patients receiving propafenone chronically have suggested no effect of propafenone HCl on sperm count.

Neuromuscular Dysfunction

Exacerbation of myasthenia gravis has been reported during propafenone therapy.

Drug Interactions

Quinidine

Small doses of quinidine completely inhibit the hydroxylation metabolic pathway, making all patients, in effect, slow metabolizers (see CLINICAL PHARMACOLOGY). There is, as yet, too little information to recommend concomitant use of propafenone and quinidine.

Local Anesthetics

Concomitant use of local anesthetics (i.e., during pacemaker implantations, surgery, or dental use) may increase the risks of central nervous system side effects.

Digitalis

Propafenone hydrochloride produces dose-related increases in serum digoxin levels ranging from about 35% at 450 mg/day to 85% at 900 mg/day of propafenone without affecting digoxin renal clearance. These elevations of digoxin levels were maintained for up to 16 months during concomitant administration. Plasma digoxin levels of patients on concomitant therapy should be measured, and digoxin dosage should ordinarily be reduced when propafenone is started, especially if a relatively large digoxin dose is used or if plasma concentrations are relatively high.

Beta-Antagonists

In a study involving healthy subjects, concomitant administration of propafenone and propranolol has resulted in substantial increases in propranolol plasma concentration and elimination half-life with no change in propafenone plasma levels from control values. Similar observations have been reported with metoprolol. Propafenone appears to inhibit the hydroxylation pathway for the two beta-antagonists (just as quinidine inhibits propafenone metabolism). Increased plasma concentrations of metoprolol could overcome its relative cardioselectivity. In propafenone clinical trials, patients who were receiving beta-blockers concurrently did not experience an increased incidence of side effects. While the therapeutic range for beta-blockers is wide, a reduction in dosage may be necessary during concomitant administration with propafenone.

Warfarin

In a study of eight healthy subjects receiving propafenone and warfarin concomitantly, mean steady-state warfarin plasma concentrations increased 39% with a corresponding increase in prothrombin times of approximately 25%. It is therefore recommended that prothrombin times be routinely monitored and the dose of warfarin be adjusted if necessary.

Cimetidine

Concomitant administration of propafenone and cimetidine in 12 healthy subjects resulted in a 20% increase in steady-state plasma concentrations of propafenone with no detectable changes in electrocardiographic parameters beyond that measured on propafenone alone.

Desipramine

Concomitant administration of propafenone and desipramine may result in elevated serum desipramine levels. Both desipramine, a tricyclic antidepressant, and propafenone are cleared by oxidative pathways of demthylation and hydroxylation carried out by the hepatic P-450 cytochrome.

Cyclosporin

Propafenone therapy may increase levels of cyclosporin.

Theophylline

Propafenone may increase theophylline concentration during concomitant therapy with the development of theophylline toxicity.

Rifampin

Rifampin may accelerate the metabolism and decrease the plasma levels and antiarrhythmic efficacy of propafenone.

Other

Limited experience with propafenone combined with calcium antagonists and diuretics has been reported without evidence of clinically significant adverse reactions. Drugs that inhibit CYP2D6, CYP1A2 and CYP3A4 might lead to increased plasma levels of propafenone. When propafenone is administered with inhibitors of these enzymes, the patients should be closely monitored and the dose adjusted accordingly.

Renal and Hepatic Toxicity in Animals

Renal changes have been observed in the rat following 6 months of oral administration of propafenone HCl at doses of 180 and 360 mg/kg/day (about 2 and 4 times, respectively, the maximum recommended human daily dose [MRHD] on a mg/m^2 basis). Both inflammatory and non-inflammatory changes in the renal tubules, with accompanying interstitial nephritis, were observed. These changes were reversible, as they were not found in rats allowed to recover for 6 weeks. Fatty degenerative changes of the liver were found in rats following longer durations of administration of propafenone HCl at a dose of 270 mg/kg/day (about 3 times the MRHD on a mg/m^2 basis). There were no renal or hepatic changes at 90 mg/kg/day (equivalent to the MRHD on a mg/m^2 basis).

Carcinogenesis, Mutagenesis, Impairment of Fertility

Lifetime maximally tolerated oral dose studies in mice (up to 360 mg/kg/day, about twice the maximum recommended human oral daily dose [MRHD] on a mg/m^2 basis) and rats (up to 270 mg/kg/day, about 3 times the MRHD on a mg/m^2 basis) provided no evidence of a carcinogenic potential for propafenone HCl.

Propafenone HCl tested negative for mutagenicity in the Ames (salmonella) test and the mouse dominant lethal test, and tested negative for clastogenicity in the Chinese hamster micronucleus test, and other in vivo tests for chromosomal aberrations in rat bone marrow and Chinese hamster bone marrow and spermatogonia.

Propafenone HCl, administered intravenously to rabbits, dogs, and monkeys has been shown to decrease spermatogenesis. These effects were reversible, were not found following oral dosing of propafenone HCl, were seen at lethal or near lethal dose levels and were not seen in rats treated either orally or intravenously (see PRECAUTIONS, Impaired Spermatogenesis). Treatment of male rabbits for 10 weeks prior to mating at an oral dose of 120 mg/kg/day (about 2.4 times the MRHD on a mg/m^2 basis) or an intravenous dose of 3.5 mg/kg/day (a spermatogenesis-impairing dose) did not result in evidence of impaired fertility. Nor was there evidence of impaired fertility when propafenone HCl was administered orally to male and female rats at dose levels up to 270 mg/kg/day (about 3 times the MRHD on a mg/m^2 basis).

Pregnancy

Teratogenic Effects

Pregnancy Category C

Propafenone HCl has been shown to be embryotoxic (decreased survival) in rabbits and rats when given in oral maternally toxic doses of 150 mg/kg/day (about 3 times the maximum recommended human dose [MRHD] on a mg/m^2 basis) and 600 mg/kg/day (about 6 times the MRHD on a mg/m^2 basis, respectively. Although maternally tolerated doses (up to 270 mg/kg/day, about 3 times the MRHD on a mg/m^2 basis) produced no evidence of embryotoxicity in rats, post-implantation loss was elevated in all rabbit treatment groups (doses as low as 15 mg/kg/day, about 1/3 the MRHD on a mg/m^2 basis). There are no adequate and well-controlled studies in pregnant women. Propafenone HCl should be used during pregnancy only if the potential benefit justifies the potential risk to the fetus.

Non-teratogenic Effects

In a study in which female rats received daily oral doses of propafenone HCl from mid-gestation through weaning of their offspring, doses as low as 90 mg/kg/day (equivalent to the MRHD on a mg/m^2 basis) produced increases in maternal deaths. Doses of 360 or more mg/kg/day (4 or more times the MRHD on a mg/m^2 basis) resulted in reductions in neonatal survival, body weight gain and physiological development.

Labor and Delivery

It is not known whether the use of propafenone during labor or delivery has immediate or delayed adverse effects on the fetus, or whether it prolongs the duration of labor or increases the need for forceps delivery or other obstetrical intervention.

Nursing Mothers

It is not known whether this drug is excreted in human milk. Because many drugs are excreted in human milk and because of the potential for serious adverse reactions in nursing infants from propafenone HCl, a decision should be made whether to discontinue nursing or to discontinue the drug, taking into account the importance of the drug to the mother.

Pediatric Use

The safety and effectiveness of propafenone HCl in pediatric patients have not been established.

Geriatric Use

Clinical studies of propafenone HCl did not include sufficient numbers of subjects aged 65 and over to determine whether they respond differently from younger subjects. Other reported clinical experience has not identified differences in responses between the elderly and younger patients. In general, dose selection for an elderly patient should be cautious, usually starting at the low end of the dosing range, reflecting the greater frequency of decreased hepatic, renal, or cardiac function, and of concomitant disease or other drug therapy.

ADVERSE REACTIONS

Adverse reactions associated with propafenone HCl occur most frequently in the gastrointestinal, cardiovascular, and central nervous systems. About 20% of patients treated with propafenone HCl have discontinued treatment because of adverse reactions.

Adverse reactions reported for >1.5% of 474 SVT patients who received propafenone in U.S. clinical trials are presented in the following table by incidence and percent discontinuation, reported to the nearest percent.

Adverse Reactions Reported for >1.5% of SVT Patients
 | Incidence (N=480) | % of Patients Who Discontinued
Unusual taste | 14% | 1.3%
Nausea and/or Vomiting | 11% | 2.9%
Dizziness | 9% | 1.7%
Constipation | 8% | 0.2%
Headache | 6% | 0.8%
Fatigue | 6% | 1.5%
Blurred Vision | 3% | 0.6%
Weakness | 3% | 1.3%
Dyspnea | 2% | 1.0%
Wide Complex Tachycardia | 2% | 1.9%
CHF | 2% | 0.6%
Bradycardia | 2% | 0.2%
Palpitations | 2% | 0.2%
Tremor | 2% | 0.4%
Anorexia | 2% | 0.2%
Diarrhea | 2% | 0.4%
Ataxia | 2% | 0.0%

Results of controlled trials in ventricular arrhythmia patients comparing adverse reaction rates on propafenone and placebo, and on propafenone and quinidine are shown in the following table. Adverse reactions reported for ≥1% of the patients receiving propafenone as shown, unless they were more frequent on placebo than propafenone. The most common events were unusual taste, dizziness, first degree AV block, intraventricular conduction delay, nausea and/or vomiting, and constipation. Headache was relatively common also, but was not increased compared to placebo.

Adverse Reactions Reported for ≥1% of Ventricular Arrhythmia Patients
 | Prop./Placebo Trials |  | Prop./Quinidine Trial
 | Prop. | Placebo | Prop. | Quinidine
 | (N=247) | (N=111) | (N=53) | (N=52)
Unusual Taste | 7% | 1% | 23% | 0%
Dizziness | 7% | 5% | 15% | 10%
First Degree AV Block | 5% | 1% | 2% | 0%
Headache(s) | 5% | 5% | 2% | 8%
Constipation | 4% | 0% | 6% | 2%
Intraventricular Conduction Delay | 4% | 0% | - | -
Nausea and/or Vomiting | 3% | 1% | 6% | 15%
Fatigue | - | - | 4% | 2%
Palpitations | 2% | 1% | - | -
Blurred Vision | 2% | 1% | 6% | 2%
Dry Mouth | 2% | 1% | 6% | 6%
Dyspnea | 2% | 3% | 4% | 0%
Abdominal Pain/Cramps | - | - | 2% | 8%
Dyspepsia | - | - | 2% | 8%
CHF | - | - | 2% | 0%
Fever | - | - | 2% | 10%
Tinnitus | - | - | 2% | 2%
Vision, Abnormal | - | - | 2% | 2%
Esophagitis | - | - | 2% | 0%
Gastroenteritis | - | - | 2% | 0%
Anxiety | 2% | 2% | - | -
Anorexia | 2% | 1% | 0% | 2%
Proarrhythmia | 1% | 0% | 2% | 0%
Flatulence | 1% | 0% | 2% | 0%
Angina | 1% | 0% | 2% | 4%
Second Degree AV Block | 1% | 0% | - | -
Bundle Branch Block | 1% | 0% | 2% | 2%
Loss of Balance | 1% | 0% | - | -
Diarrhea | 1% | 1% | 6% | 39%

Adverse reactions reported for ≥1% of 2,127 ventricular arrhythmia patients who received propafenone in U.S. clinical trials are presented in the following table by propafenone daily dose. The most common adverse reactions in controlled clinical trials appeared dose-related (but note that most patients spent more time at the larger doses), especially dizziness, nausea and/or vomiting, unusual taste, constipation, and blurred vision. Some less common reactions may also have been dose-related such as first degree AV block, congestive heart failure, dyspepsia, and weakness. The principal causes of discontinuation were the most common events and are shown in the table.

Adverse Reactions Reported for ≥1% of Ventricular Arrhythmia Patients N=2127
 | Incidence by Total Daily Dose |  |  | Total Incidence | % of Pts. Who Discont.
 | 450 mg | 600 mg | ≥900 mg | Total Incidence | % of Pts. Who Discont.
 | (N=1430) | (N=1337) | (N=1333) | (N=2127)
Dizziness | 4% | 7% | 11% | 13% | 2.4%
Nausea and/or Vomiting | 2% | 6% | 9% | 11% | 3.4%
Unusual Taste | 3% | 5% | 6% | 9% | 0.7%
Constipation | 2% | 4% | 5% | 7% | 0.5%
Fatigue | 2% | 3% | 4% | 6% | 1.0%
Dyspnea | 2% | 2% | 4% | 5% | 1.6%
Proarrhythmia | 2% | 2% | 3% | 5% | 4.7%
Angina | 2% | 2% | 3% | 5% | 0.5%
Headache(s) | 2% | 3% | 3% | 5% | 1.0%
Blurred Vision | 1% | 2% | 3% | 4% | 0.8%
CHF | 1% | 2% | 3% | 4% | 1.4%
Ventricular Tachycardia | 1% | 2% | 3% | 3% | 1.2%
Dyspepsia | 1% | 2% | 3% | 3% | 0.9%
Palpitations | 1% | 2% | 3% | 3% | 0.5%
Rash | 1% | 1% | 2% | 3% | 0.8%
AV Block, First Degree | 1% | 1% | 2% | 3% | 0.3%
Diarrhea | 1% | 2% | 2% | 3% | 0.6%
Weakness | 1% | 2% | 2% | 2% | 0.7%
Dry Mouth | 1% | 1% | 1% | 2% | 0.2%
Syncope/Near Syncope | 1% | 1% | 1% | 2% | 0.7%
QRS Duration, Increased | 1% | 1% | 2% | 2% | 0.5%
Chest Pain | 1% | 1% | 1% | 2% | 0.2%
Anorexia | 1% | 1% | 2% | 2% | 0.4%
Abdominal Pain, Cramps | 1% | 1% | 1% | 2% | 0.4%
Ataxia | 0% | 1% | 2% | 2% | 0.2%
Insomnia | 0% | 1% | 1% | 2% | 0.3%
Premature Ventricular Contraction(s) | 1% | 1% | 1% | 2% | 0.1%
Bradycardia | 1% | 1% | 1% | 2% | 0.5%
Anxiety | 1% | 1% | 1% | 2% | 0.6%
Edema | 1% | 0% | 1% | 1% | 0.2%
Tremor(s) | 0% | 1% | 1% | 1% | 0.3%
Diaphoresis | 1% | 0% | 1% | 1% | 0.3%
Bundle Branch Block | 0% | 1% | 1% | 1% | 0.5%
Drowsiness | 1% | 1% | 1% | 1% | 0.2%
Atrial Fibrillation | 1% | 1% | 1% | 1% | 0.4%
Flatulence | 0% | 1% | 1% | 1% | 0.1%
Hypotension | 0% | 1% | 1% | 1% | 0.4%
Intraventricular Conduction Delay | 0% | 1% | 1% | 1% | 0.1%
Pain, Joints | 0% | 0% | 1% | 1% | 0.1%

In addition, the following adverse reactions were reported less frequently than 1% either in clinical trials or in marketing experience (adverse events for marketing experience are given in italics). Causality and relationship to propafenone therapy cannot necessarily be judged from these events.

Cardiovascular System: Atrial flutter, AV dissociation, cardiac arrest, flushing, hot flashes, sick sinus syndrome, sinus pause or arrest, supraventricular tachycardia.

Nervous System: Abnormal dreams, abnormal speech, abnormal vision, apnea, coma, confusion, depression, memory loss, numbness, paresthesias, psychosis/mania, seizures (0.3%), tinnitus, unusual smell sensation, vertigo.

Gastrointestinal: A number of patients with liver abnormalities associated with propafenone therapy have been reported in post-marketing experience. Some appeared due to hepatocellular injury, some were cholestatic and some showed a mixed picture. Some of these reports were simply discovered through clinical chemistries, others because of clinical symptoms including fulminant hepatitis and death. One case was rechallenged with a positive outcome. Cholestasis (0.1%), elevated liver enzymes (alkaline phosphatase, serum transaminases) (0.2%), gastroenteritis, hepatitis (0.03%).

Hematologic: Agranulocytosis, anemia, bruising, granulocytopenia, increased bleeding time, leukopenia, purpura, thrombocytopenia.

Other: Alopecia, eye irritation, hyponatremia/inappropriate ADH secretion, impotence, increased glucose, kidney failure, positive ANA (0.7%), lupus erythematosis, muscle cramps, muscle weakness, nephrotic syndrome, pain, pruritus.

OVERDOSAGE

The symptoms of overdosage, which are usually most severe within 3 hours of ingestion, may include hypotension, somnolence, bradycardia, intra-atrial and intraventricular conduction disturbances, and rarely convulsions and high grade ventricular arrhythmias. Defibrillation as well as infusion of dopamine and isoproterenol have been effective in controlling rhythm and blood pressure. Convulsions have been alleviated with intravenous diazepam. General supportive measures such as mechanical respiratory assistance and external cardiac massage may be necessary.

DOSAGE AND ADMINISTRATION

The dose of propafenone HCl must be individually titrated on the basis of response and tolerance. It is recommended that therapy be initiated with 150 mg propafenone given every eight hours (450 mg/day). Dosage may be increased at a minimum of 3 to 4 day intervals to 225 mg every 8 hours (675 mg/day) and, if necessary, to 300 mg every 8 hours (900 mg/day). The usefulness and safety of dosages exceeding 900 mg per day have not been established. In those patients in whom significant widening of the QRS complex or second or third degree AV block occurs, dose reduction should be considered.

As with other antiarrhythmic agents, in the elderly or in ventricular arrhythmia patients with marked previous myocardial damage, the dose of propafenone HCl should be increased more gradually during the initial phase of treatment.

HOW SUPPLIED

Propafenone hydrochloride tablets are supplied as follows:

Propafenone hydrochloride tablets 150 mg, white, round, scored, film-coated, debossed MP 511

Bottles of 20 | NDC 54868-4770-2
Bottles of 30 | NDC 54868-4770-5
Bottles of 60 | NDC 54868-4770-1
Bottles of 90 | NDC 54868-4770-4
Bottles of 100 | NDC 54868-4770-3

Propafenone hydrochloride tablets 225 mg, white, round, scored, film-coated, debossed MP 512

Bottles of 30 | NDC 54868-5950-1
Bottles of 90 | NDC 54868-5950-0
Bottles of 60 | NDC 54868-5950-2

STORAGE AND HANDLING

Store at 20° to 25°C (68° to 77°F).

[See USP Controlled Room Temperature]

DISPENSE IN TIGHT, LIGHT-RESISTANT CONTAINER.

Manufactured by:
MUTUAL PHARMACEUTICAL CO., INC.
Philadelphia, PA 19124 USA

Rev 01, May 2009

Relabeling and Repackaging by:

Physicians Total Care, Inc.
Tulsa, OK 74146

PRINCIPAL DISPLAY PANEL - 150 mg label

PROPAFENONE
HYDROCHLORIDE
TABLETS
150 mg

Rx only

PRINCIPAL DISPLAY PANEL - 225 mg label

PROPAFENONE
HYDROCHLORIDE
TABLETS
225 mg

Rx only